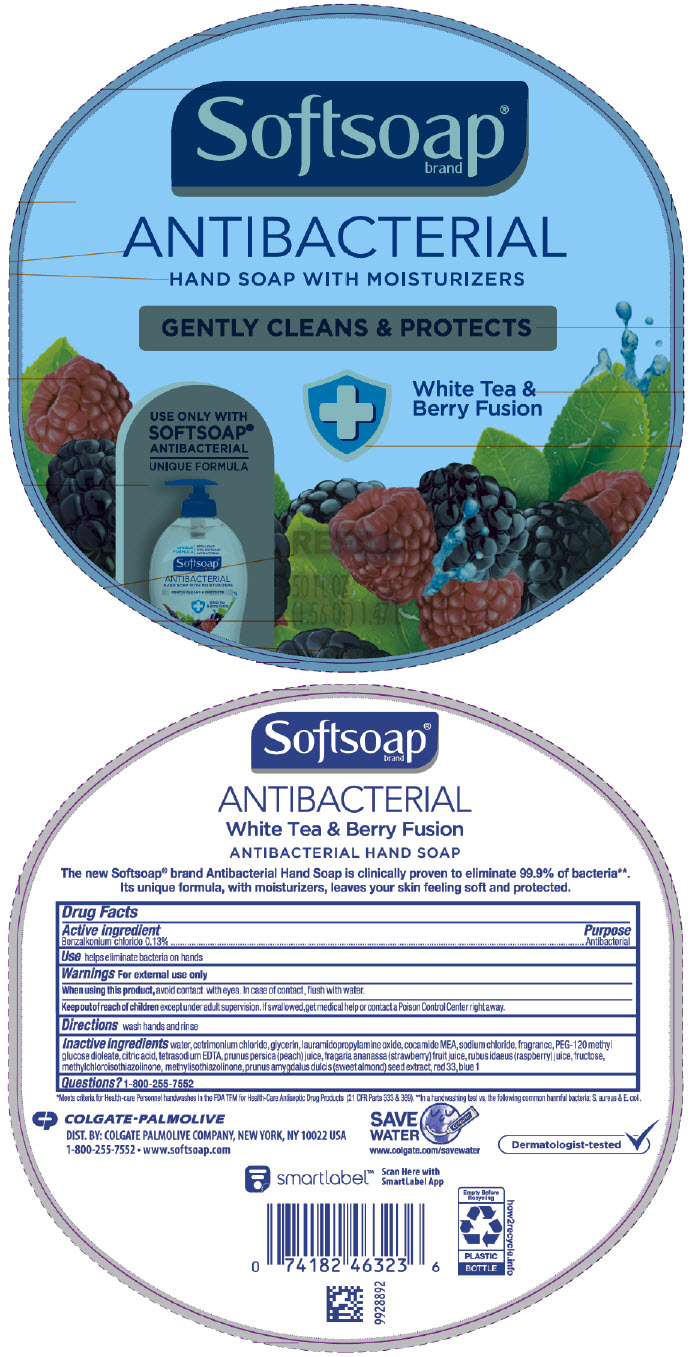 DRUG LABEL: SoftSoap Antibacterial with moisturizers White Tea and Berry Fusion
NDC: 35000-081 | Form: LIQUID
Manufacturer: COLGATE PALMOLIVE COMPANY
Category: otc | Type: HUMAN OTC DRUG LABEL
Date: 20191210

ACTIVE INGREDIENTS: BENZALKONIUM CHLORIDE 1.33 mg/1 mL
INACTIVE INGREDIENTS: WATER; CETRIMONIUM CHLORIDE; GLYCERIN; LAURAMIDOPROPYLAMINE OXIDE; COCO MONOETHANOLAMIDE; SODIUM CHLORIDE; PEG-120 METHYL GLUCOSE DIOLEATE; CITRIC ACID MONOHYDRATE; EDETATE SODIUM; PEACH JUICE; STRAWBERRY JUICE; RASPBERRY JUICE; FRUCTOSE; METHYLCHLOROISOTHIAZOLINONE; METHYLISOTHIAZOLINONE; ALMOND; D&C RED NO. 33; FD&C BLUE NO. 1

SoftSoap® Antibacterial Hand Soap with moisturizers White Tea and Berry Fusion 1.47L (50oz)

Drug Facts

Active ingredient

Benzalkonium chloride 0.13%

Purpose

Antibacterial

Use

helps eliminate bacteria on hands

Warnings

For external use only

When using this product, avoid contact with eyes. In case of contact, flush with water.

Keep out of reach of children except under adult supervision. If swallowed, get medical help or contact a Poison Control Center right away.

Directions

wash hands and rinse

Inactive ingredients

water, cetrimonium chloride, glycerin, lauramidopropylamine oxide, cocamide MEA, sodium chloride, fragrance, PEG-120 methyl glucose dioleate, citric acid, tetrasodium EDTA, prunus persica (peach) juice, fragaria ananassa (strawberry) fruit juice, rubus idaeus (raspberry) juice, fructose, methylchloroisothiazolinone, methylisothiazolinone, prunus amygdalus dulcis (sweet almond) seed extract, red 33, blue 1

Questions?

1-800-255-7552

DIST. BY: COLGATE PALMOLIVE COMPANY, NEW YORK, NY 10022 USA

PRINCIPAL DISPLAY PANEL - 1478 mL Bottle Label

Softsoap®
brand

ANTIBACTERIAL
HAND SOAP WITH MOISTURIZERS

GENTLY CLEANS & PROTECTS

White Tea &
Berry Fusion

USE ONLY WITH
SOFTSOAP®
ANTIBACTERIAL
UNIQUE FORMULA